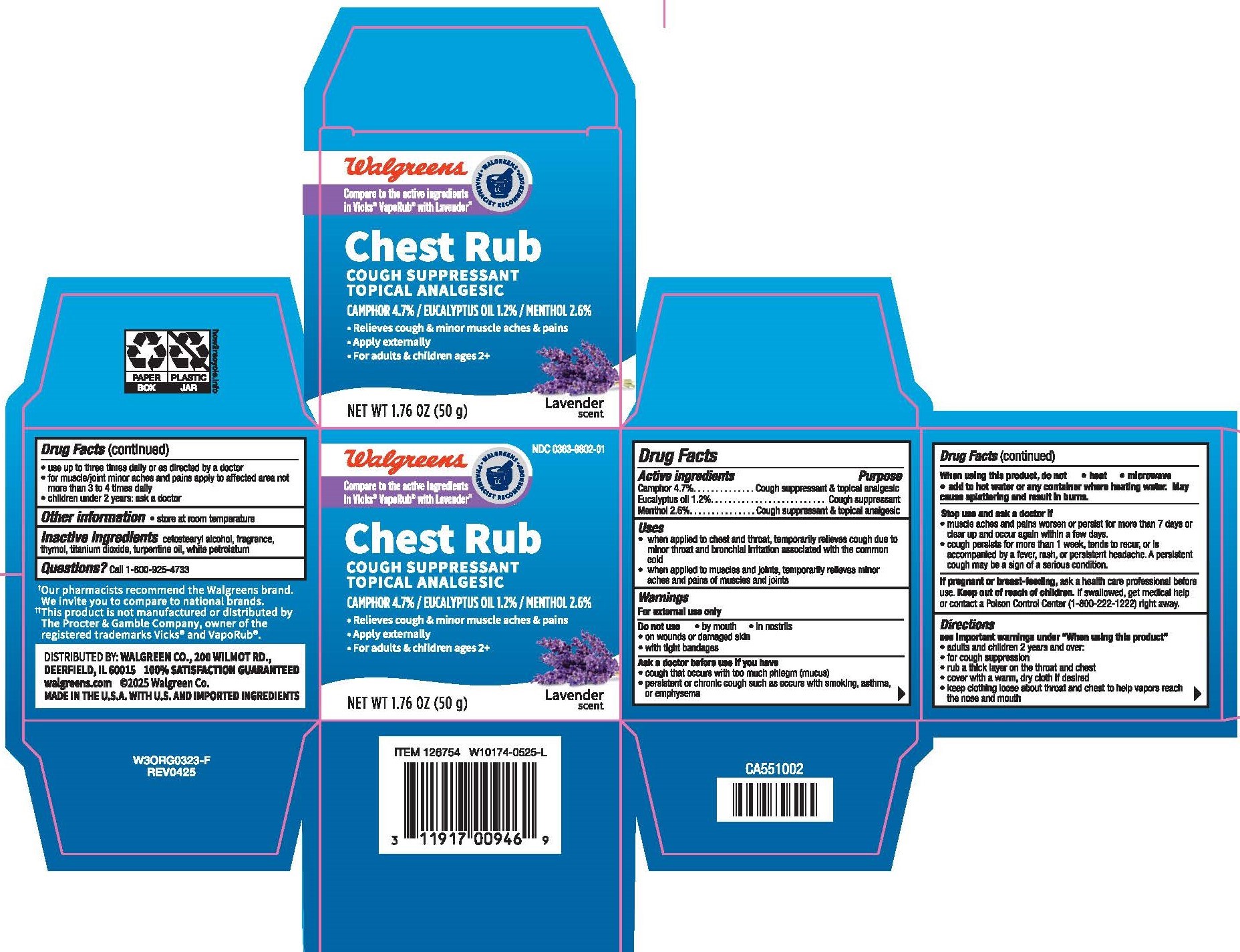 DRUG LABEL: Walgreens Lavender Chest Rub
NDC: 0363-9802 | Form: OINTMENT
Manufacturer: Walgreen Company
Category: otc | Type: HUMAN OTC DRUG LABEL
Date: 20250731

ACTIVE INGREDIENTS: CAMPHOR (NATURAL) 47 mg/1 g; MENTHOL 26 mg/1 g; EUCALYPTUS OIL 12 mg/1 g
INACTIVE INGREDIENTS: WHITE PETROLATUM; FRAGRANCE 13576; THYMOL; TURPENTINE OIL; CETOSTEARYL ALCOHOL; TITANIUM DIOXIDE

Drug Facts - Walgreens Lavender Chest Rub

Active ingredients

Camphor 4.7%

Eucalyptus oil 1.2%

Menthol 2.6%

Purpose

Camphor – Cough suppressant/topical analgesic
Eucalyptus oil – Cough suppressant
Menthol – Cough suppressant/topical analgesic

Uses

- when applied to chest and throat, temporarily relieves cough due to minor throat and bronchial irritation associated with the common cold
- when applied to muscles and joints, temporarily relieves minor aches and pains of muscles and joints

Warnings

For external use only

Do not use

- by mouth
- in nostrils
- on wounds or damaged skin
- with tight bandages

Ask a doctor before use if you have

- cough that occurs with too much phlegm (mucus)
- persistent or chronic cough such as occurs with smoking, asthma or emphysema

When using this product, do not

- heat
- microwave
- add to hot water or any container where heating water. May cause splattering and result in burns.

Stop use and ask a doctor if

- muscle aches and pains worsen or persist for more than 7 days or clear up and occur again within a few days.
- cough persists for more than 1 week, tends to recur, or is accompanied by a fever, rash, or persistent headache. A persistent cough may be a sign of a serious condition.

If pregnant or breast-feeding,

ask a health professional before use.

Keep out of reach of children.

If swallowed, get medical help or contact a Poison Control Center (1-800-222-1222) right away.

Directions

see important warning under "When using this product"

- adults and children 2 years and over:
- for cough suppression
- rub a thick layer on the throat and chest for cough
- cover with a warm, dry cloth if desired
- keep clothing loose about throat and chest to help vapors reach the nose and mouth
- use up to 3 times daily or as directed by a doctor
- for muscle/joint minor aches and pains apply to affected area not more than 3 to 4 times daily
- children under 2 years: ask a doctor

Other Information

- store at room temperature

Inactive Ingredients

cetostearyl alcohol, fragrance, thymol, titanium dioxide, turpentine oil, white petrolatum

Questions?

Call 1-800-925-4733

Package Label Principal Display Panel